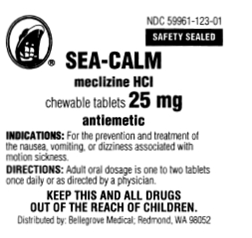 DRUG LABEL: SEA-CALM
NDC: 59961-123 | Form: TABLET, CHEWABLE
Manufacturer: Bellegrove
Category: otc | Type: HUMAN OTC DRUG LABEL
Date: 20100309

ACTIVE INGREDIENTS: MECLIZINE HYDROCHLORIDE 25 mg/1 1
INACTIVE INGREDIENTS: SILICON DIOXIDE; FD&C RED NO. 40; LACTOSE; CROSPOVIDONE; CROSCARMELLOSE SODIUM; RASPBERRY; VANILLA; SACCHARIN SODIUM; MAGNESIUM STEARATE; STEARIC ACID

Drug Facts

Active ingredient

Meclizine Hydrochloride 25 mg

Purpose

Antiemetic

Uses

For the prevention and treatment of nausea, vomiting or dizziness associated with motion sickness

Warnings

Do not take this product if you have asthma, glaucoma, emphysema, chronic pulmonary disease, shortness of breath, difficulty in breathing, or difficulty in urination due to enlargement of the prostate gland, unless directed by a physician. Do not give to children under 12 years of age unless directed by a physician. May cause drowsiness; alcohol, sedatives, and tranquilizers may increase the drowsiness effect. Avoid alcoholic beverages while taking this product. Do not take this product if you are taking sedatives or tranquilizers, without first consulting your physician. Use caution when driving a motor vehicle or operating machinery. As with any drug, if you are pregnant or nursing a baby, seek the advice of a health professional before using this product.

Directions

Adult oral dosage is one to two tablets once daily or as directed by a physician.

Inactive ingredients

Crosscarmellose Sodium, Crospovidone, FD&C Red #40 Lake, Lactose, Magnesium Stearate, Raspberry Flavor, Silica, Sodium Saccharin, Stearic Acid and Vanilla Flavor.